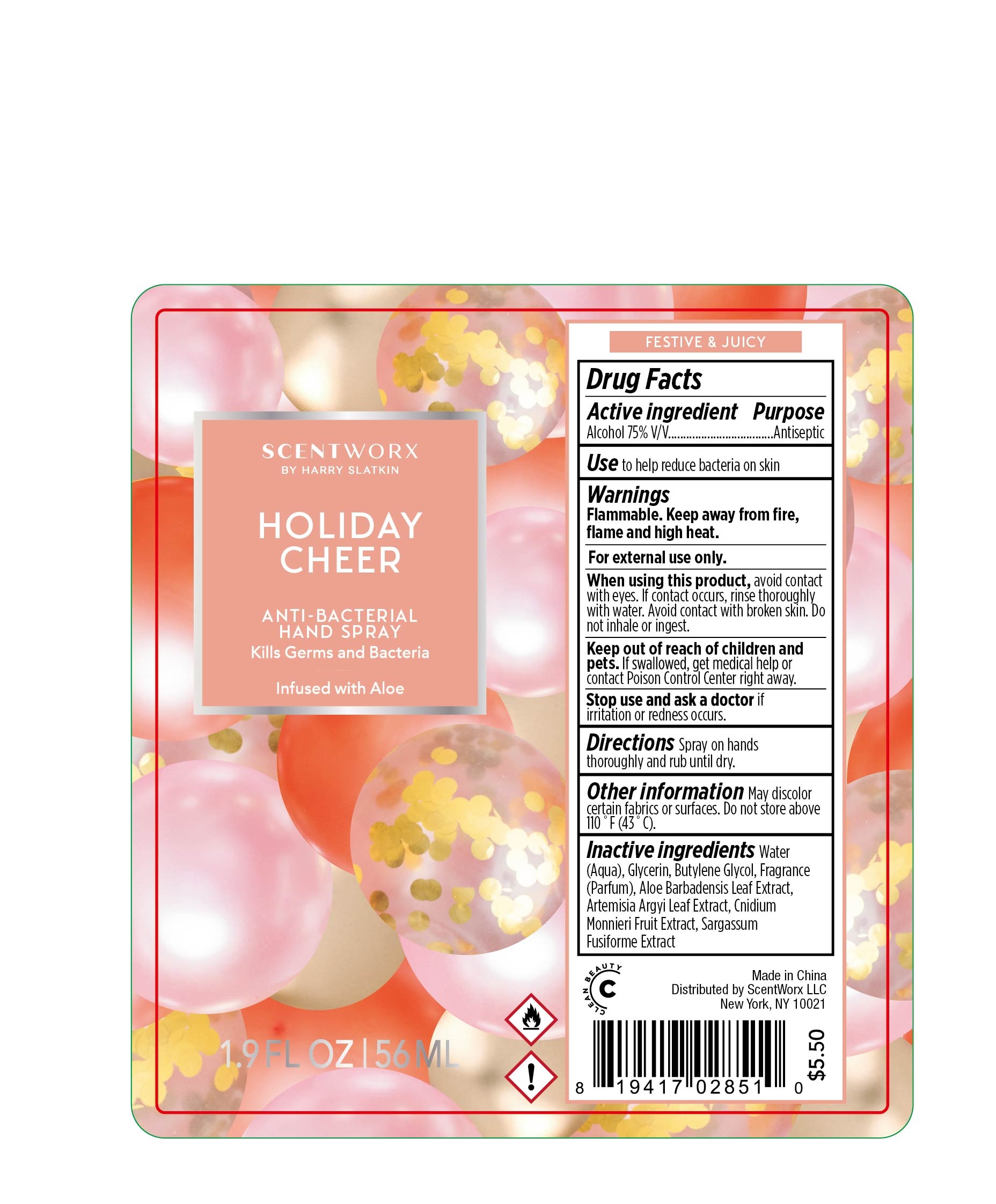 DRUG LABEL: Hand Sanitizer
NDC: 81282-049 | Form: SPRAY
Manufacturer: HS HomeWorx LLC
Category: otc | Type: HUMAN OTC DRUG LABEL
Date: 20210518

ACTIVE INGREDIENTS: ALCOHOL 75 mL/100 mL
INACTIVE INGREDIENTS: GLYCERIN 1 mL/100 mL; WATER 23 mL/100 mL; BUTYLENE GLYCOL 1 mL/100 mL

This is a hand sanitizer manufactured according to the Temporary Policy for Preparation of Certain Alcohol-Based Hand Sanitizer Products During the Public Health Emergency (CoViD-19); Guidance for Industry.

The hand sanitizer is manufactured using only the following United States Pharmacopoeia (USP) grade ingredients in the preparation of the product (percentage in final product formulation) consistent with World Health Organization (WHO) recommendations:

1. Alcohol (ethanol) (USP or Food Chemical Codex (FCC) grade) (80%, volume/volume (v/v)) in an aqueous solution denatured according to Alcohol and Tobacco Tax and Trade Bureau regulations in 27 CFR part 20.
2. Glycerol (1.45% v/v).
3. Hydrogen peroxide (0.125% v/v).
4. Sterile distilled water or boiled cold water.

The firm does not add other active or inactive ingredients. Different or additional ingredients may impact the quality and potency of the product.

Active Ingredient(s)

Alcohol 75% v/v. Purpose: Antiseptic

Purpose

Antiseptic

Use

to help reduce bacteria on skin

Warnings

For external use only. Flammable. Keep away from fire, flame and high heat

When using this product avoid contact with eyes. If contact occurs, rinse eyes thoroughly with water.
Do not inhale or ingest. Avoid contact with broken skin.

Stop use and ask a doctor if irritation or redness occurs.

Keep out of reach of children. If swallowed, get medical help or contact a Poison Control Center right away.

Directions

- Spray on hands thoroughly and rub until dry.

Other information

- Do not store above 110F (43C)
- May discolor certain fabrics or surfaces.

Inactive ingredients

Aqua (Water), Glycerin, Butylene Glycol, Fragrance, Aloe Barbadensis Leaf Extract, Artemisia Argyi Leaf Extract, Cnidium Monnieri Fruit Extract, Sargassum Fusiforme Extract

Package Label - Principal Display Panel

56 mL NDC: 81282-049-01